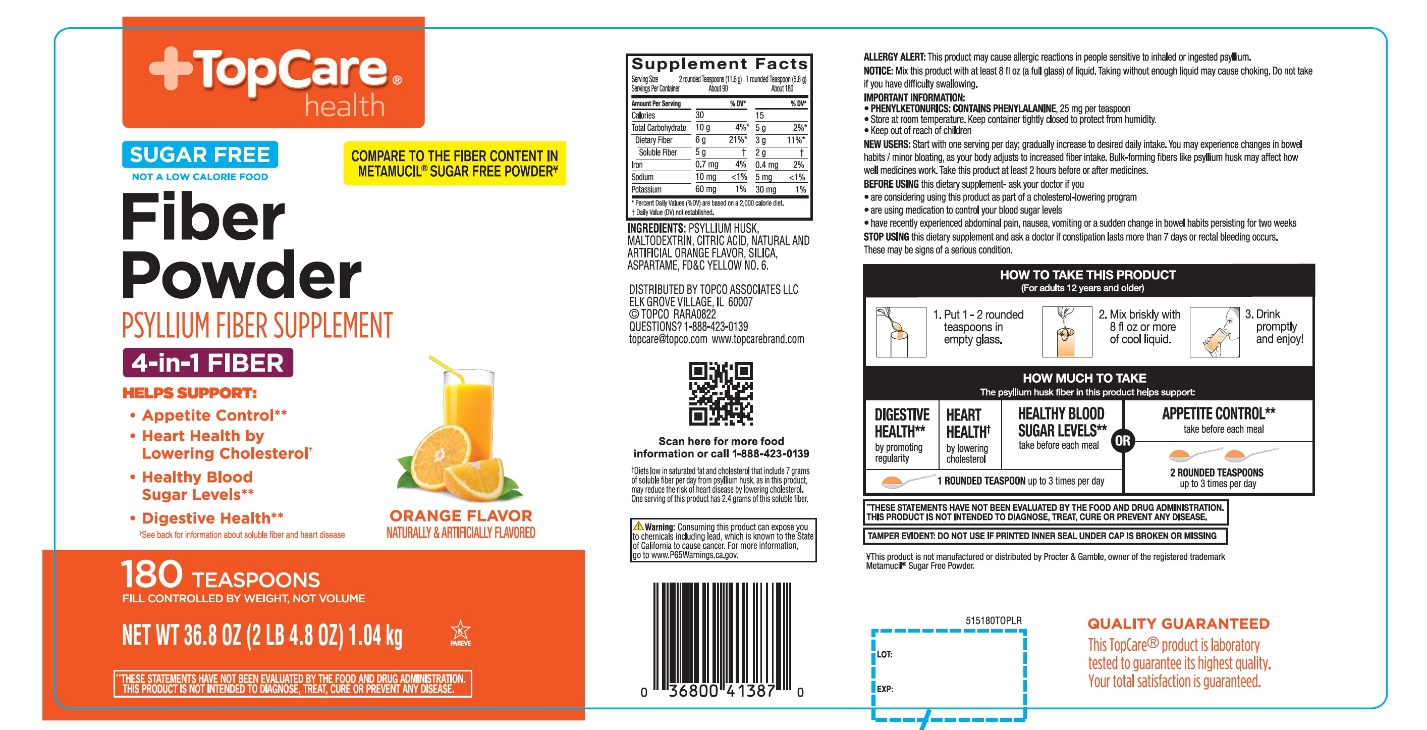 DRUG LABEL: Topco Fiber Therapy

NDC: 36800-558 | Form: POWDER
Manufacturer: TOPCO ASSOCIATES LLC
Category: otc | Type: HUMAN OTC DRUG LABEL
Date: 20251110

ACTIVE INGREDIENTS: PSYLLIUM HUSK 3.4 g/5.79 g
INACTIVE INGREDIENTS: ASPARTAME; ANHYDROUS CITRIC ACID; FD&C YELLOW NO. 6; MALTODEXTRIN; SILICON DIOXIDE

TopCare®health™PSYLLIUM HUSK Orange Flavor Sugar free 180 Teaspoon Doses

Drug Facts

Active ingredient: (in each TEASPOON)

Psyllium husk approximately 3.4 g

Purpose

Bulk-forming Laxative

Uses:

- for relief of occasional constipation (irregularity)
- generally produces bowel movement in 12-72 hours

Warnings:

Choking:

Taking this product without adequate fluid may cause it to swell and block your throat or esophagus and may cause choking. Do not take this product if you have difficulty in swallowing. If you experience chest pain, vomiting, or difficulty in swallowing or breathing after taking this product, seek immediate medical attention.

Allergy alert:

This product may cause allergic reaction in people sensitive to inhaled or ingested psyllium.

Ask a doctor before use if you have

- a sudden change in bowel habits persisting for 2 weeks
- abdominal pain, nausea or vomiting

Stop use and ask a doctor if

- constipation lasts more than 7 days
- rectal bleeding occurs

These may be signs of a serious condition.

Keep out of reach of children.In case of overdose, get medical help or contact a Poison Control Center right away at 1-800-222-1222.

Directions:

Put one dose into an empty glass. Mix this product (child or adult dose) with at least 8 ounces (a full glass) of water or other fluid. Taking this product without enough liquid may cause choking. See choking warning. Stir briskly and drink promptly. If mixture thickens, add more liquid and stir.

Adults & children 12 years & older: | 1 rounded TEASPOON in 8 oz. of liquid at the first sign of irregularity. Can be taken up to 3 times daily.
Children 6-11 yrs : | ½ adult dose in 8 oz. of liquid, up to 3 times daily
Children under 6 yrs: | Consult a doctor

Bulk-forming fibers like psyllium husk may affect how well other medicines work. If you are taking a prescription medicine by mouth, take this product at least 2 hours before or 2 hours after the prescribed medicine.

New Users:

Start with 1 serving per day; gradually increase to 3 doses per day as necessary. You may initially experience changes in bowel habits or minor bloating, as your body adjusts to increased fiber intake.

Other information:

- each teaspoon contains: potassium 35 mg; sodium 5 mg
- PHENYLKETONURICS: CONTAINS PHENYLALANINE,25 mg per teaspoon
- contains a therapeutic fiber
- store at room temperature. Keep the container tightly closed to protect from humidity

Inactive ingredients:

aspartame, citric acid, FD&C Yellow 6, maltodextrin, natural and artificial orange flavor, silica.

Questions or comments?

1-888-423-0139

PRINCIPAL DISPLAY PANEL

NDC 36800-558-80

COMPARE TO THE METAMUCIL®4 IN 1 MULTIHEALTH FIBER! ™*

SUGAR FREE (NOT A LOW CALORIE FOOD)

Fiber Therapy

PSYLLIUM HUSK DAILY FIBER SUPPLEMENT THERAPY FOR REGULARITY

- Helps lower cholesterolto promote heart health†
- Promotes digestive health**
- Helps maintain healthy blood sugarlevels as part of your diet **
- Orange Smooth Fiber Powder
- Gluten free

ORANGE FLAVOR

NATURALLY AND ARTIFICIALLY FLAVORED

180 TEASPOON‡Doses

FILL CONTROLLED BY WEIGHT, NOT VOLUME

NET WT 36.8 OZ (2 LB 4.8 OZ) 1.04 kg

K

PAREVE

QUALITY GURANTEED

‡Serving size varies See DIRECTIONS on back panel for more information

†See back for information about soluble fiber and heart disease.

**THESE STATEMENTS HAVE NOT BEEN EVALUATED BY THE FOOD AND DRUG ADMINISTRATION. THIS PRODUCT IS NOT INTENDED TO DIAGNOSE, TREAT, CURE OR PREVENT ANY DISEASE.

TAMPER EVIDENT: DO NOT USE IF PRINTED INNER SEAL UNDER CAP IS BROKEN OR MISSING

*This product is not manufactured or distributed by Procter & Gamble, the distributor of Metamucil®4 in 1 MultiHealth Fiber!™.

This product has a low glycemic index, a measure of the effect of dietary carbohydrates on blood sugar levels.

This Top Care product is laboratory tested to guarantee its highest quality. You total satisfaction is guaranteed.

DISTRIBUTED BY TOPCO ASSOCIATES LLC, ELK GROVE VILLAGE, IL 60007

© TOPCO RARA1217

QUESTIONS? 1-888-423-0139

topcare@topco.comwww.topcarebrand.com